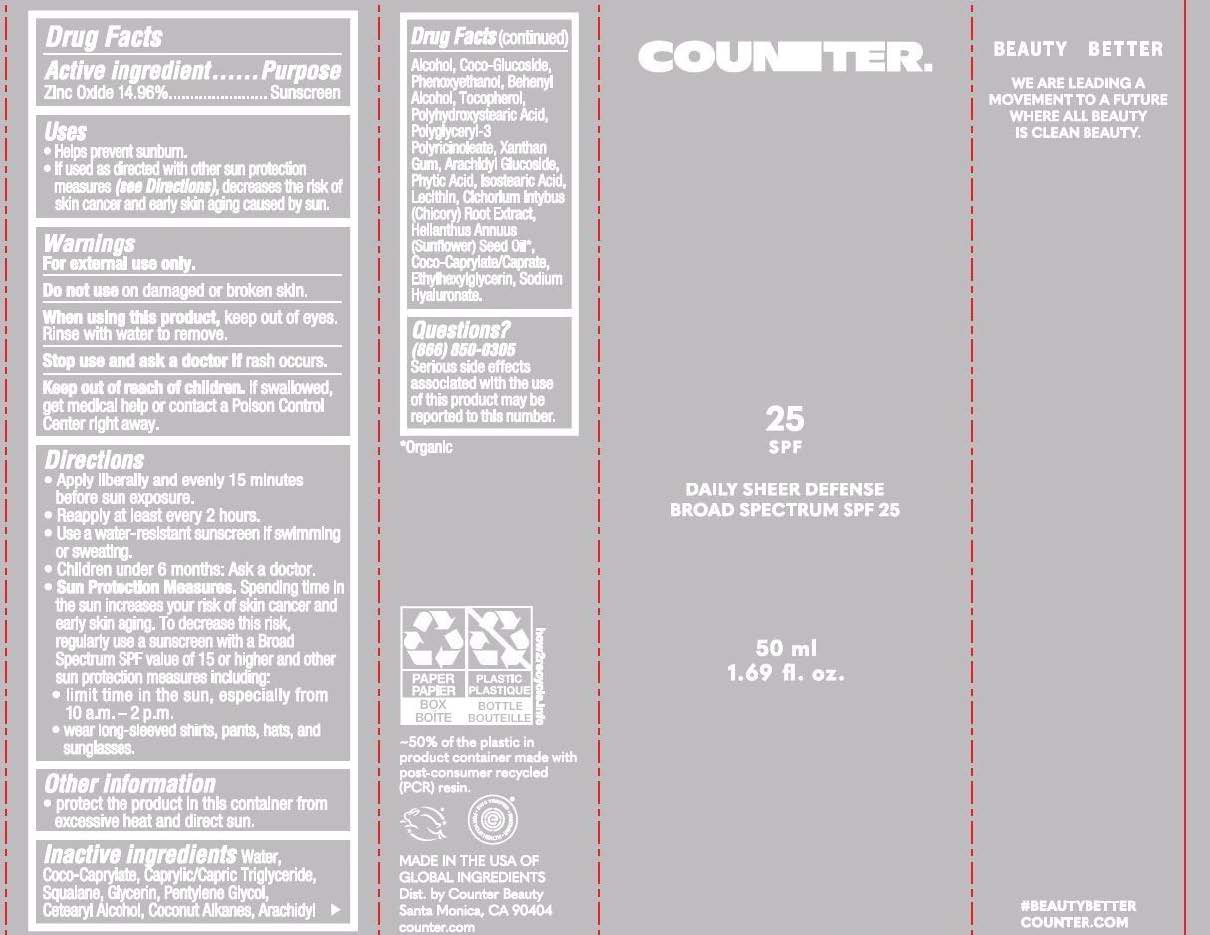 DRUG LABEL: Counter Beauty Daily Sheer Defense SPF 25
NDC: 84435-100 | Form: LOTION
Manufacturer: G2G Ventures, PBC
Category: otc | Type: HUMAN OTC DRUG LABEL
Date: 20250717

ACTIVE INGREDIENTS: ZINC OXIDE 14.96 g/100 g
INACTIVE INGREDIENTS: POLYGLYCERYL-3 PENTARICINOLEATE; TOCOPHEROL; WATER; CETEARYL ALCOHOL; ARACHIDYL GLUCOSIDE; POLYHYDROXYSTEARIC ACID (2300 MW); CAPRYLIC/CAPRIC TRIGLYCERIDE; ARACHIDYL ALCOHOL; ISOSTEARIC ACID; COCO-CAPRYLATE; COCONUT ALKANES; CICHORIUM INTYBUS (CHICORY) ROOT OLIGOSACCHARIDES; XANTHAN GUM; COCO-CAPRYLATE/CAPRATE; BEHENYL ALCOHOL; LECITHIN, SOYBEAN; PHYTIC ACID; GLYCERIN; PENTYLENE GLYCOL; COCO GLUCOSIDE; PHENOXYETHANOL; ETHYLHEXYLGLYCERIN; SQUALANE; HELIANTHUS ANNUUS (SUNFLOWER) SEED OIL; SODIUM HYALURONATE

Counter Beauty Daily Sheer Defense SPF 25

ACTIVE INGREDIENT

Zinc Oxide 14.96%

PURPOSE

Sunscreen

INDICATIONS AND USAGE

- Helps prevent sunburn.
- If used as directed with other sun protection measure (see Directions), decreases the risk of skin cancer and early skin aging caused by sun.

WARNINGS

For external use only.

DO NOT USE

On damaged or broken skin.

STOP USE

rash occurs.

WHEN USING

Keep out of eyes. Rinse with water to remove.

KEEP OUT OF REACH OF CHILDREN

If swalowed, get medical help or contact Poison Control Center right away.

DOSAGE AND ADMINISTRATION

- Apply liberally 15 minutes before sun exposure.
- Reapply at least every 2 hours.
- Use a water-resitant sunscreen if swimming or sweating.
- Children under 6: Ask a doctor.
  - Sun Protection Measures. Spending time in the sun increases your risk of skin cancer and early skin aging. To decrease this risk, regularly use a sunscreen with a Broad Spectrum SPF value of 15 or higher and other sun protection measures including:
  - limit time in the sun, especially from 10 a.m.-2 p.m.
  - wear long-sleeved shirts, pants, hats, and sunglasses.

OTHER SAFETY INFORMATION

- protect the product in this container from excessive heat and direct sun.

INACTIVE INGREDIENT

Water, Coco-Caprylate, Caprylic/Capric Triglyceride, Glycerin, Squalane, Pentylene Glycol, Cetearyl Alcohol, Coconut Alkanes, Arachidyl Alchohol, Coco-Glucoside, Phenoxyethanol, Behenyl Alcohol, Arachidyl Glucoside, Isostearic Acid, Lecithin, Polyglyceryl-3 Polyricinoleate, Polyhydroxystearic Acid, Xanthan Gum, Tocopherol, Phytic Acid, Helianthus Annuus (Sunflower) Seed oil, Cichorium Intybus (Chicory) Root Extract, Coco-Caprylate/Caprate, Ethylhexylglycerin, Sodium Hyaluronate.